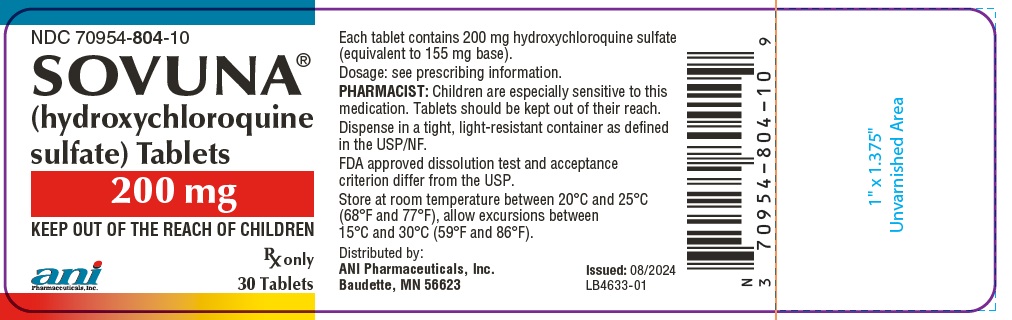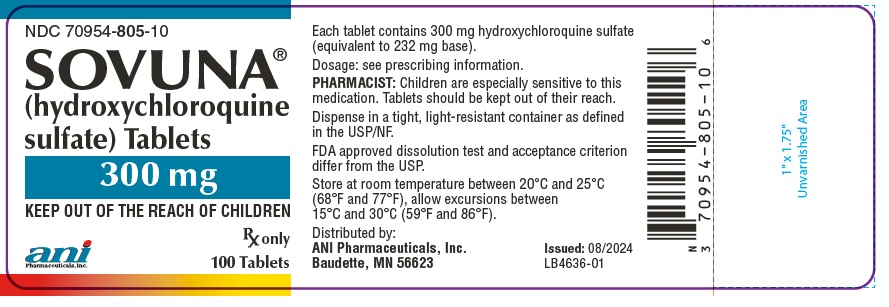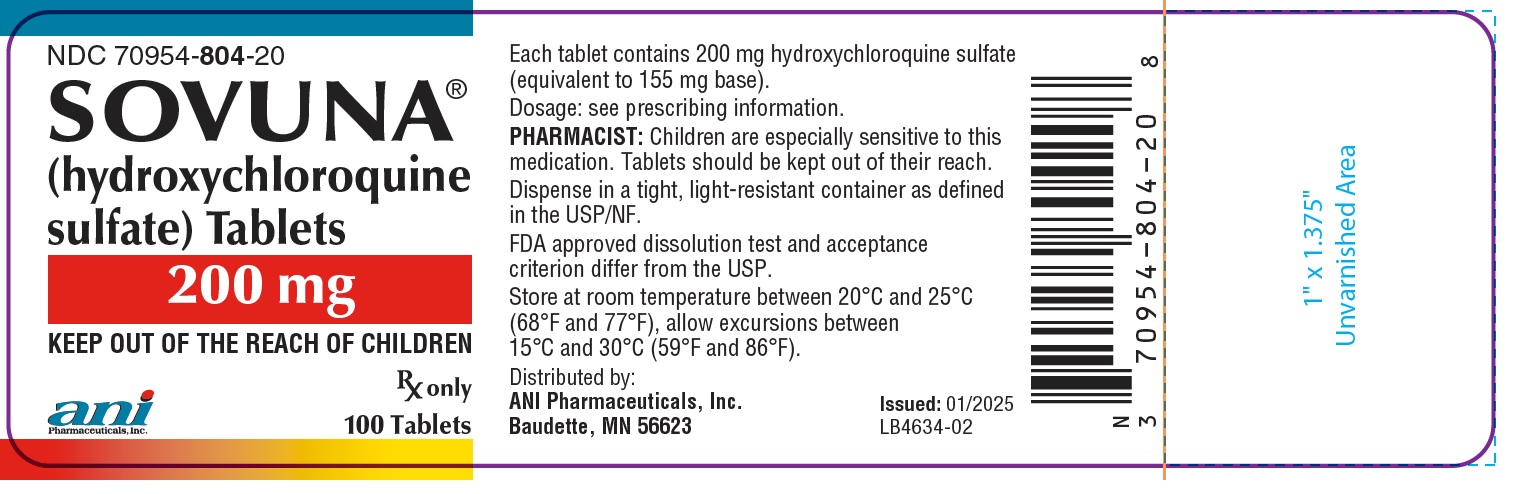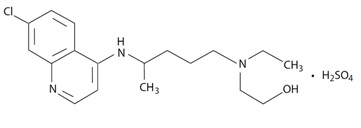 DRUG LABEL: SOVUNA
NDC: 70954-804 | Form: TABLET, FILM COATED
Manufacturer: ANI Pharmaceuticals, Inc.
Category: prescription | Type: Human Prescription Drug Label
Date: 20241008

ACTIVE INGREDIENTS: HYDROXYCHLOROQUINE SULFATE 200 mg/1 1
INACTIVE INGREDIENTS: LACTOSE MONOHYDRATE; STARCH, CORN; CROSCARMELLOSE SODIUM; SUCRALOSE; HYPROMELLOSE, UNSPECIFIED; TALC; MAGNESIUM STEARATE; POLYSORBATE 80; TITANIUM DIOXIDE; POLYETHYLENE GLYCOL, UNSPECIFIED; TRIACETIN; WATER

HIGHLIGHTS OF PRESCRIBING INFORMATION

These highlights do not include all the information needed to use SOVUNA safely and effectively. See full prescribing information for SOVUNA.
SOVUNA® (hydroxychloroquine sulfate) tablets, for oral use
Initial U.S. Approval: 1955

1 INDICATIONS & USAGE

SOVUNA is an antimalarial and antirheumatic indicated for the:

- Treatment of uncomplicated malaria due to Plasmodium falciparum, Plasmodium malariae, Plasmodium ovale, and Plasmodium vivax in adult and pediatric patients. (1.1)
- Prophylaxis of malaria in geographic areas where chloroquine resistance is not reported in adult and pediatric patients. (1.1)
- Treatment of rheumatoid arthritis in adults. (1.2)
- Treatment of systemic lupus erythematosus in adults. (1.3)
- Treatment of chronic discoid lupus erythematosus in adults. (1.4)

Limitations of Use (1.1):

SOVUNA is not recommended for the:

- Treatment of complicated malaria.
- Treatment of chloroquine or hydroxychloroquine-resistant strains of Plasmodium species.
- Treatment of malaria acquired in geographic areas where chloroquine resistance occurs or when the Plasmodium species has not been identified.
- Prophylaxis of malaria in geographic areas where chloroquine resistance occurs.
- Prevention of relapses of P. vivax or P. ovale because it is not active against the hypnozoite liver stage forms of these parasites. For radical cure of P. vivax and P. ovale infections, concomitant therapy with an 8-aminoquinoline drug is necessary.

2 DOSAGE & ADMINISTRATION

Malaria in Adult and Pediatric Patients (2.2):

- Prophylaxis: Begin weekly doses 2 weeks prior to travel to the endemic area, continue weekly doses while in the endemic area, and continue the weekly doses for 4 weeks after leaving the endemic area:

Adults: 400 mg once a week

Pediatric patients weighing greater than or equal to 23 kg: 6.5 mg/kg actual body weight up to 400 mg, once a week

- Treatment of Uncomplicated Malaria: See Full Prescribing Information (FPI) for complete dosing information.

Rheumatoid Arthritis in Adults (2.3):

- Initial dosage: 400 mg to 600 mg daily
- Chronic dosage: 200 mg, 300 mg or 400 mg once daily (or in two divided doses)

Systemic Lupus Erythematosus in Adults (2.4):

- 200 mg, 300 mg or 400 mg once daily (or in two divided doses)

Chronic Discoid Lupus Erythematosus in Adults (2.5):

200 mg or 400 mg once daily (or in two divided doses)

3 DOSAGE FORMS & STRENGTHS

- Tablets: 200 mg of hydroxychloroquine sulfate
- Tablets: 300 mg of hydroxychloroquine sulfate; functionally scored (3)

4 CONTRAINDICATIONS

- Patients with hypersensitivity to 4-aminoquinoline compounds (4)

5 WARNINGS AND PRECAUTIONS

- Cardiomyopathy and Ventricular Arrhythmias: Fatal or life-threatening cardiomyopathy and ventricular arrhythmias were reported. (5.1)
- Retinal Toxicity: Irreversible retinal damage is related to cumulative dosage and treatment duration. Baseline retinal exam and exams during treatment are recommended. (5.2)
- Serious Skin Reactions: Stevens Johnson syndrome, toxic epidermal necrolysis, drug reaction with eosinophilia and systemic symptoms, acute generalized exanthematous pustulosis have been reported. (5.3)
- Worsening of Psoriasis: Avoid in patients with psoriasis. (5.4)
- Risks Associated with Use in Porphyria: Avoid in patients with porphyria. Hepatotoxicity was reported in patients with porphyria cutanea tarda (5.5)
- Hematologic Toxicity: Discontinue if myelosuppression occurs. (5.6)
- Renal Toxicity: Consider phospholipidosis as a possible cause of renal injury in patients with underlying connective tissue disorders. Discontinue SOVUNA if renal toxicity is suspected or demonstrated by tissue biopsy in any organ system. (5.1, 5.8, 5.11)

6 ADVERSE REACTIONS

The most common adverse reactions reported are: nausea, vomiting, diarrhea, and abdominal pain. (6)

To report SUSPECTED ADVERSE REACTIONS, contact ANI Pharmaceuticals, Inc. at 1-855-204-1431 or the FDA at 1-800-FDA-1088 or www.fda.gov/medwatch.

7 DRUG INTERACTIONS

- Drugs Prolonging QT Interval and Other Arrhythmogenic Drugs. (7.1)
- See FPI for more important drug interactions. (7)

FULL PRESCRIBING INFORMATION

1 INDICATIONS & USAGE

1.1 Malaria

SOVUNA is indicated in adult and pediatric patients for the:

- Treatment of uncomplicated malaria due to Plasmodium falciparum, Plasmodium malariae, Plasmodium vivax, and Plasmodium ovale.
- Prophylaxis of malaria in geographic areas where chloroquine resistance is not reported.

Limitations of Use:

SOVUNA is not recommended for:

- Treatment of complicated malaria.
- Treatment of malaria by chloroquine or hydroxychloroquine-resistant strains of Plasmodium species [see Microbiology (12.4)].
- Treatment of malaria acquired in geographic areas where chloroquine resistance occurs or when the Plasmodium species has not been identified.
- Prophylaxis of malaria in geographic areas where chloroquine resistance occurs.
- Prevention of relapses of P. vivax or P. ovale because it is not active against the hypnozoite liver stage forms of these parasites. For radical cure of P. vivax and P. ovale infections, concomitant therapy with an 8-aminoquinoline drug is necessary [see Microbiology (12.4)].

For the most current information about drug resistance, refer to the latest recommendations from the Center for Disease Control and Prevention.^1

1.2 Rheumatoid Arthritis

SOVUNA is indicated for the treatment of acute and chronic rheumatoid arthritis in adults.

1.3 Systemic Lupus Erythematosus

SOVUNA is indicated for the treatment of systemic lupus erythematosus in adults.

1.4 Chronic Discoid Lupus Erythematosus

SOVUNA is indicated for the treatment of chronic discoid lupus erythematosus in adults.

2 DOSAGE & ADMINISTRATION

2.1 Important Administration Instructions

Administer SOVUNA orally with food or milk. Do not crush the tablets.

2.2 Dosage for Malaria in Adult and Pediatric Patients

SOVUNA is not recommended in pediatric patients less than 23 kg because the lowest possible dose of 150 mg (half of the scored 300 mg tablet) exceeds the recommended dose for these patients.

Prophylaxis

Treatment must start 2 weeks before travel to an endemic area. Advise the patient to take the prophylaxis dosage once a week, staring 2 weeks prior to travel to the endemic area, on the same day every week, continuing the same weekly dose while in the endemic area, and for 4 weeks after leaving the endemic area. The recommended prophylaxis dosage is:

- Adult patients: 400 mg once a week
- Pediatric patients weighing greater than or equal to 23 kg: 6.5 mg/kg actual body weight (up to 400 mg) once a week

Treatment of Uncomplicated Malaria

The dosages for the treatment of uncomplicated malaria are:

- Adult patients: Administer 800 mg initially; subsequently administer 400 mg at 6 hours, 24 hours, and 48 hours after the initial dose (total dosage = 2,000 mg).
- Pediatric patients weighing greater than or equal to 23 kg: Administer 13 mg/kg (up to 800 mg) initially; subsequently administer 6.5 mg/kg (up to 400 mg) at 6 hours, 24 hours, and 48 hours after the initial dose (total dosage = 31 mg/kg - up to 2,000 mg).

For radical cure of P. vivax and P. ovale infections, concomitant therapy with an 8aminoquinoline drug is necessary [see Microbiology (12.4)].

2.3 Dosage for Rheumatoid Arthritis in Adults

The recommended dosage is:

- Initial dosage: 400 mg to 600 mg daily as a single daily dose or two divided doses. The action of hydroxychloroquine is cumulative and may require weeks to months for maximum therapeutic effect. Daily doses exceeding 5 mg/kg (actual weight) of hydroxychloroquine sulfate increase the incidence of retinopathy [see Warnings and Precautions (5.2)].
- Chronic dosage: 200 mg, 300 mg or 400 mg daily, as a single dose or two divided doses.

Corticosteroids, salicylates, and other antirheumatic agents may be used concomitantly with SOVUNA.

2.4 Dosage for Systemic Lupus Erythematosus in Adults

The recommended dosage is 200 mg, 300 mg or 400 mg daily, as a single dose or two divided doses

2.5 Dosage for Chronic Discoid Lupus Erythematosus in Adults

The recommended dosage is 200 mg or 400 mg daily, as a single dose or two divided doses.

3 DOSAGE FORMS & STRENGTHS

SOVUNA tablets are available in the following strengths:

- 200 mg of hydroxychloroquine sulfate: white to off-white, capsule-shaped, film-coated tablets, debossed with "172" on one side and plain on the other side.

- 300 mg of hydroxychloroquine sulfate: white to off-white, functionally scored, capsule-shaped, film-coated tablets, debossed with "1" on left side of the score and "71" on right side of the score and plain on the other side. The scoring allows the tablet to be divided into two equal halves containing 150 mg each.

4 CONTRAINDICATIONS

SOVUNA is contraindicated in patients with known hypersensitivity to 4-aminoquinoline compounds.

5 WARNINGS AND PRECAUTIONS

5.1 Cardiomyopathy and Ventricular Arrhythmias

Fatal and life-threatening cases of cardiotoxicity, including cardiomyopathy, have been reported in patients treated with SOVUNA. Signs and symptoms of cardiac compromise have occurred during acute and chronic SOVUNA treatment. In multiple cases, endomyocardial biopsy showed association of the cardiomyopathy with phospholipidosis in the absence of inflammation, infiltration, or necrosis. Drug-induced phospholipidosis may occur in other organ systems [see Warnings and Precautions (5.8, 5.11)].

Patients may present with ventricular hypertrophy, pulmonary hypertension and conduction disorders including sick sinus syndrome. ECG findings include atrioventricular, right or left bundle branch block.

SOVUNA has a potential to prolong the QT interval. Ventricular arrhythmias (including torsades de pointes) have been reported in SOVUNA-treated patients. The magnitude of QT prolongation may increase with increasing concentrations of the drug. Therefore, the recommended dose should not be exceeded [see Adverse Reactions (6), Overdosage (10)]. Avoid SOVUNA administration in patients with congenital or documented acquired QT prolongation and/or known risk factors for prolongation of the QT interval such as:

- Cardiac disease, e.g., heart failure, myocardial infarction.
- Proarrhythmic conditions, e.g., bradycardia (< 50 bpm).
- History of ventricular dysrhythmias.
- Uncorrected hypokalemia and/or hypomagnesemia.
- Concomitant administration with QT interval prolonging agents as this may lead to an increased risk for ventricular arrhythmias [see Drug Interactions (7.1)].

Therefore, SOVUNA is not recommended in patients taking other drugs that have the potential to prolong the QT interval. Correct electrolyte imbalances prior to use. Monitor cardiac function as clinically indicated during SOVUNA therapy. Discontinue SOVUNA if cardiotoxicity is suspected or demonstrated by tissue biopsy.

5.2 Retinal Toxicity

Irreversible retinal damage was observed in some patients treated with hydroxychloroquine sulfate and it is related to cumulative dosage and treatment duration. In patients of Asian descent, retinal toxicity may first be noticed outside the macula.

Risk factors for retinal damage include daily hydroxychloroquine sulfate dosages ≥5 mg/kg of actual body weight, durations of use greater than five years, renal impairment, use of concomitant drug products such as tamoxifen citrate, and concurrent macular disease.

Within the first year of starting SOVUNA, a baseline ocular examination is recommended including best corrected distance visual acuity (BCVA), an automated threshold visual field (VF) of the central 10 degrees (with retesting if an abnormality is noted), and spectral domain ocular coherence tomography (SD-OCT). For patients at higher risk of retinal damage, monitoring should include annual examinations which include BCVA, VF and SD-OCT. For patients without significant risk factors, annual retinal exams can usually be deferred until five years of treatment. In patients of Asian descent, it is recommended that visual field testing be performed in the central 24 degrees instead of the central 10 degrees.

If ocular toxicity is suspected, discontinue SOVUNA and monitor the patient closely given that retinal changes and visual disturbances may progress even after cessation of therapy.

5.3 Serious Skin Reactions

Serious adverse reactions have been reported with the use of SOVUNA including Stevens-Johnson syndrome (SJS), toxic epidermal necrolysis (TEN), drug reaction with eosinophilia and systemic symptoms (DRESS syndrome), acute generalized exanthematous pustulosis (AGEP). Monitor for serious skin reactions, especially in patients receiving a drug that may also induce dermatitis. Advise patients to seek medical attention promptly if they experience signs and symptoms of serious skin reactions such as blisters on the skin, eyes, lips or in the mouth, itching or burning, with or without fever [see Warnings and Precautions (5.4,5.5), Adverse Reactions (6)]. Discontinue SOVUNA if these severe reactions occur.

5.4 Worsening of Psoriasis

Administration of SOVUNA to patients with psoriasis may precipitate a severe flare-up of psoriasis. Avoid SOVUNA in patients with psoriasis, unless the benefit to the patient outweighs the possible risk.

5.5 Risks Associated with Use in Porphyria

Administration of SOVUNA to patients with porphyria may exacerbate porphyria. Avoid SOVUNA in patients with porphyria.

Hepatotoxicity Associated with Porphyria Cutanea Tarda

Cases of hepatotoxicity have been reported when hydroxychloroquine was used in patients with porphyria cutanea tarda (PCT). Patients received dosages ranging from 200 mg twice weekly to 400 mg daily. Most of the PCT-related cases presented with marked elevations in transaminases (>20 times upper limit of the reference range) within days to a month of hydroxychloroquine initiation. In some cases, PCT was diagnosed only after the occurrence of treatment-induced liver injury, when hydroxychloroquine was prescribed for an approved indication. Some of the cases were associated with other risk factors for hepatic injury (e.g., alcohol use, concomitant hepatotoxic medications).

Measure liver tests promptly in patients who report symptoms that may indicate liver injury, such as fatigue, rash, nausea, dark urine, or jaundice. In this clinical context, if the patient is found to have abnormal serum liver tests (e.g., ALT level greater than three times the upper limit of the reference range, total bilirubin greater than two times the upper limit of the reference range), interrupt treatment with SOVUNA, and investigate further to establish the probable cause.

The safety and effectiveness of SOVUNA for the treatment of PCT have not been established and SOVUNA is not approved for this use.

5.6 Hematologic Toxicity

SOVUNA may cause myelosuppression including aplastic anemia, agranulocytosis, leukopenia, or thrombocytopenia. Monitor blood cell counts periodically in patients on prolonged SOVUNA therapy. If the patient develops myelosuppression which cannot be attributable to the disease, discontinue the drug.

5.7 Hemolytic Anemia Associated with G6PD Deficiency

Hemolysis has been reported in patients with glucose-6-phosphate dehydrogenase (G6PD) deficiency. Monitor for hemolytic anemia as this can occur, particularly in association with other drugs that cause hemolysis.

5.8 Skeletal Muscle Myopathy or Neuropathy

Skeletal muscle myopathy or neuropathy leading to progressive weakness and atrophy of proximal muscle groups, depressed tendon reflexes, and abnormal nerve conduction, have been reported. Muscle and nerve biopsies have shown associated phospholipidosis. Drug-induced phospholipidosis may occur in other organ systems [see Warnings and Precautions

(5.1, 5.11)].

Assess muscle strength and deep tendon reflexes periodically in patients on long-term therapy with SOVUNA. Discontinue SOVUNA if muscle or nerve toxicity is suspected or demonstrated by tissue biopsy.

5.9 Neuropsychiatric Reactions Including Suicidality

Suicidal behavior, suicidal ideation, and other neuropsychiatric adverse reactions have been reported in patients treated with SOVUNA [see Adverse Reactions (6)].

Neuropsychiatric adverse reactions typically occurred within the first month after the start of treatment with hydroxychloroquine and have been reported in patients with and without a prior history of psychiatric disorders.

The risks and benefits of continued treatment with SOVUNA should be assessed for patients who develop these symptoms. Given the long half-life of the drug, some patients may require several weeks off drug for symptoms to partially or fully abate.

Advise patients to contact their healthcare provider promptly if they experience new or worsening neuropsychiatric symptoms such as depression, suicidal thoughts or behavior, or mood changes.

5.10 Hypoglycemia

SOVUNA can cause severe and potentially life-threatening hypoglycemia, in the presence or absence of antidiabetic agents [see Drug Interactions (7)]. Measure blood glucose in patients presenting with clinical symptoms suggestive of hypoglycemia and as adjust the antidiabetic treatment as necessary. Warn SOVUNA-treated patients about the risk of hypoglycemia and educate them on the signs and symptoms of hypoglycemia; diabetic patients should monitor their blood sugar levels. Advise patients to seek medical attention if they develop any signs and symptoms of hypoglycemia.

5.11 Renal Toxicity

Proteinuria with or without moderate reduction in glomerular filtration rate have been reported with the use of SOVUNA.

Renal biopsy showed phospholipidosis without immune deposits, inflammation, and/or increased cellularity. Physicians should consider phospholipidosis as a possible cause of renal injury in patients with underlying connective tissue disorders who are receiving SOVUNA. Drug-induced phospholipidosis may occur in other organ systems [see Warnings and Precautions (5.1, 5.8)]. Discontinue SOVUNA if renal toxicity is suspected or demonstrated by tissue biopsy.

6 ADVERSE REACTIONS

The following adverse reactions are described in greater detail in other sections:

- Cardiomyopathy and Ventricular Arrhythmias [see Warnings and Precautions (5.1)]
- Retinal Toxicity [see Warnings and Precautions (5.2)]
- Serious Skin Reactions [see Warnings and Precautions (5.3)]
- Worsening of Psoriasis [see Warnings and Precautions (5.4)]
- Risks Associated with Use in Porphyria [see Warnings and Precautions (5.5)]
- Hematologic Toxicity [see Warnings and Precautions (5.6)]
- Hemolytic Anemia Associated with G6PD [see Warnings and Precautions (5.7)]
- Skeletal Muscle Myopathy or Neuropathy [see Warnings and Precautions (5.8)]
- Neuropsychiatric Reactions Including Suicidality [see Warnings and Precautions (5.9)]
- Hypoglycemia [see Warnings and Precautions (5.10)]
- Renal Toxicity [see Warnings and Precautions (5.11)]

The following adverse reactions have been identified during post-approval use of 4 aminoquinoline drugs, including SOVUNA. Because these reactions are reported voluntarily from a population of uncertain size, it is not always possible to reliably estimate their frequency or establish a causal relationship to drug exposure:

- Blood and lymphatic system disorders: Bone marrow depression, anemia, aplastic anemia, agranulocytosis, leukopenia, thrombocytopenia
- Cardiac disorders: Cardiomyopathy, cardiac failure, QT-interval prolongation, ventricular tachycardia, torsades de pointes, atrioventricular block, bundle branch block, sick sinus syndrome, pulmonary hypertension
- Ear and labyrinth disorders: Vertigo, tinnitus, nystagmus, sensorineural hearing loss
- Eye disorders: Retinopathy, retinal pigmentation changes (typically bull’s eye appearance), visual field defects (paracentral scotomas), macular degeneration, corneal edema, corneal opacities, decreased dark adaptation
- Gastrointestinal disorders: Nausea, vomiting, diarrhea, abdominal pain
- General disorders: Fatigue
- Hepatobiliary disorders: Abnormal liver function tests, fulminant hepatic failure
- Immune system disorders: Urticaria, angioedema, bronchospasm
- Metabolism and nutrition disorders: Anorexia, hypoglycemia, weight loss
- Musculoskeletal and connective tissue disorders: Proximal myopathy, depressed tendon reflexes, abnormal nerve conduction
- Nervous system disorders: Ataxia, dizziness, headache, seizure, extrapyramidal disorders (dystonia, dyskinesia, tremor)
- Neuropsychiatric disorders: Affect/emotional lability, irritability, nervousness, psychosis, suicidal ideation, suicidal behavior, depression, hallucinations, anxiety, agitation, confusion, delusions, paranoia, mania and sleep disorders (insomnia, night terrors, nightmares)

- Skin and subcutaneous tissue disorders: Alopecia, hair color changes, rash, pruritus, photosensitivity, psoriasis exacerbation, hyperpigmentation, exfoliative dermatitis, erythema multiforme, acute generalized exanthematous pustulosis, Drug Rash with Eosinophilia and Systemic Symptoms (DRESS syndrome), Stevens-Johnson syndrome (SJS), toxic epidermal necrolysis (TEN)

7 DRUG INTERACTIONS

7.1 Drugs Prolonging QT Interval and Other Arrhythmogenic Drugs

SOVUNA prolongs the QT interval. There may be an increased risk of inducing ventricular arrhythmias if SOVUNA is used concomitantly with other arrhythmogenic drugs. Therefore, SOVUNA is not recommended in patients taking other drugs that have the potential to prolong the QT interval or are arrhythmogenic [see Warnings and Precautions (5.1)].

7.2 Insulin or Other Antidiabetic Drugs

SOVUNA may enhance the effects of insulin and antidiabetic drugs, and consequently increase the hypoglycemic risk. Therefore, a decrease in dosage of insulin and other antidiabetic drugs may be necessary [see Warnings and Precautions (5.10)].

7.3 Drugs that Lower the Seizure Threshold

SOVUNA can lower the seizure threshold. Co-administration of SOVUNA with other antimalarials known to lower the seizure threshold (e.g., mefloquine) may increase the risk of seizures.

7.4 Antiepileptics

The activity of antiepileptic drugs might be impaired if co-administered with SOVUNA.

7.5 Methotrexate

Concomitant use of SOVUNA and methotrexate may increase the incidence of adverse reactions.

7.6 Cyclosporine

An increased plasma cyclosporin level was reported when cyclosporin and SOVUNA were co-administered. Monitor serum cyclosporine levels closely in patients receiving combined therapy.

7.7 Digoxin

Concomitant SOVUNA and digoxin therapy may result in increased serum digoxin levels. Monitor serum digoxin levels closely in patients receiving combined therapy.

7.8 Cimetidine

Concomitant use of cimetidine resulted in a 2-fold increase of exposure of chloroquine, which is structurally related to hydroxychloroquine. Interaction of cimetidine with hydroxychloroquine cannot be ruled out. Avoid concomitant use of cimetidine.

7.9 Rifampicin

Lack of efficacy of hydroxychloroquine was reported when rifampicin was concomitantly administered. Avoid concomitant use of rifampicin.

7.10 Praziquantel

Chloroquine has been reported to reduce the bioavailability of praziquantel. Interaction of praziquantel with hydroxychloroquine cannot be ruled out.

7.11 Antacids and kaolin

Antacids and kaolin can reduce absorption of chloroquine; an interval of at least 4 hours between intake of these agents and chloroquine should be observed. Interaction of antacids and kaolin with hydroxychloroquine cannot be ruled out.

7.12 Ampicillin

In a study of healthy volunteers, chloroquine significantly reduced the bioavailability of ampicillin. Interaction of ampicillin with hydroxychloroquine cannot be ruled out.

8 USE IN SPECIFIC POPULATIONS

8.1 Pregnancy

Pregnancy Exposure Registry

There is a pregnancy exposure registry that monitors pregnancy outcomes in women exposed to SOVUNA during pregnancy. Encourage patients to register by contacting 1-877-311-8972.

Risk Summary

Prolonged clinical experience over decades of use and available data from published epidemiologic and clinical studies with hydroxychloroquine use in pregnant women have not identified a drug-associated risk of major birth defects, miscarriage, or adverse maternal, or fetal outcomes (see Data). There are risks to the mother and fetus associated with untreated or increased disease activity from malaria, rheumatoid arthritis, and systemic lupus erythematosus in pregnancy (see Clinical Considerations). Animal reproduction studies were not conducted with hydroxychloroquine.

The estimated background risk of major birth defects and miscarriage for the indicated populations is unknown. All pregnancies have a background risk of birth defect, loss, or other adverse outcomes. In the US general population, the estimated background risk of major birth defects and miscarriage in clinically recognized pregnancies is 2-4% and 15-20%, respectively.

Clinical Considerations

Disease-Associated Maternal and/or Embryo-Fetal Risk

Malaria: Malaria during pregnancy increases the risk for adverse pregnancy outcomes, including maternal anemia, prematurity, spontaneous abortion, and stillbirth.

Rheumatoid Arthritis: Published data suggest that increased disease activity is associated with the risk of developing adverse pregnancy outcomes in women with rheumatoid arthritis Adverse pregnancy outcomes include preterm delivery (before 37 weeks of gestation), low birth weight (less than 2500 g) infants, and small for gestational age at birth.

Systemic Lupus Erythematosus: Pregnant women with systemic lupus erythematosus, especially those with increased disease activity, are at increased risk of adverse pregnancy outcomes, including spontaneous abortion, fetal death, preeclampsia, preterm birth, and intrauterine growth restriction. Passage of maternal auto-antibodies across the placenta may result in neonatal illness, including neonatal lupus and congenital heart block.

Data

Human Data

Data from published epidemiologic and clinical studies have not established an association with SOVUNA use during pregnancy and major birth defects, miscarriage, or adverse maternal or fetal outcomes. Hydroxychloroquine readily crosses the placenta with cord blood levels corresponding to maternal plasma levels. No retinal toxicity, ototoxicity, cardiotoxicity, or growth and developmental abnormalities have been observed in children who were exposed to hydroxychloroquine in utero. Available epidemiologic and clinical studies have methodological limitations including small sample size and study design.

8.2 Lactation

Risk Summary

Published lactation data report that hydroxychloroquine is present in human milk at low levels. No adverse reactions have been reported in breastfed infants. No retinal toxicity, ototoxicity, cardiotoxicity, or growth and developmental abnormalities have been observed in children who were exposed to hydroxychloroquine through breastmilk. There is no information on the effect of hydroxychloroquine on milk production. The developmental and health benefits of breastfeeding should be considered along with the mother’s clinical need for SOVUNA and any potential adverse effects on the breastfed child from SOVUNA or from the underlying maternal condition.

8.4 Pediatric Use

The safety and effectiveness of SOVUNA have been established in pediatric patients for the treatment of uncomplicated malaria due to P. falciparum, P. malariae, P. vivax, and P. ovale, as well as for the prophylaxis of malaria in geographic areas where chloroquine resistance is not reported. However, this product cannot be directly administered to pediatric patients weighing less than 23 kg because the lowest possible dose of 150 mg (half of the scored 300 mg tablet) exceeds the recommended dose for these patients [see Dosage and Administration (2.2)].

The safety and effectiveness of SOVUNA have not been established in pediatric patients for the treatment of rheumatoid arthritis, chronic discoid lupus erythematosus, or systemic lupus erythematosus.

8.5 Geriatric Use

Clinical trials of SOVUNA did not include sufficient numbers of patients 65 years of age and older to determine whether they respond differently from younger adult patients. Nevertheless, this drug is known to be substantially excreted by the kidney, and the risk of toxic reactions to this drug may be greater in patients with impaired renal function. In general, dose selection in geriatric patients should start with the lowest recommended dose, taking into consideration the greater frequency of decreased hepatic, renal or cardiac function, and of concomitant disease or other drug therapy.

8.6 Patients with Renal or Hepatic Disease

A reduction in the dosage of SOVUNA may be necessary in patients with hepatic or renal disease.

10 OVERDOSAGE

SOVUNA overdosage symptoms have an onset within 1–3 hours of ingestion. The following have been reported with SOVUNA overdosage:

- Cardiovascular toxicity, including QRS or QTc prolongation, ventricular tachycardia, ventricular fibrillation, torsade de pointes, atrioventricular block, cardiac arrest and death.
- Life-threatening hypotension is common.
- Severe hypokalemia secondary to an intracellular shift is common in severe toxicity.
- Central nervous system (CNS) depression, seizures, visual disturbances, transient blindness, and coma may occur.

Gastrointestinal decontamination procedures warrant consideration in patients that present within the first hour post-ingestion. If the level of consciousness rapidly deteriorates in severe poisoning, consider intubation before gastrointestinal decontamination procedures. Monitor plasma potassium levels and manage accordingly. Hemofiltration, hemodialysis, and hemoperfusion are not of benefit.

Consider contacting a poison center (1-800-221-2222) or a medical toxicologist for overdosage management recommendations.

11 DESCRIPTION

SOVUNA contains hydroxychloroquine sulfate, an antimalarial and antirheumatic drug, chemically described as 2-[[4-[(7-Chloro-4- quinolyl)amino]pentyl]ethylamino] ethanol sulfate (1:1) with the molecular formula C18H26ClN3O•H2SO4. The molecular weight of hydroxychloroquine sulfate is 433.95. Its structural formula is:

Hydroxychloroquine sulfate is a white or off-white crystalline powder, freely soluble in water; practically soluble in alcohol, chloroform, and ether.

Each SOVUNA (hydroxychloroquine sulfate) Tablet, 200 mg for oral administration contains 200 mg hydroxychloroquine sulfate, equivalent to 155 mg base.

Each SOVUNA (hydroxychloroquine sulfate) Tablet, 300 mg for oral administration contains 300 mg hydroxychloroquine sulfate, equivalent to 232 mg base.

Inactive Ingredients: Corn starch, croscarmellose sodium,hypromellose, lactose monohydrate, magnesium stearate, polyethylene glycol, polysorbate 80, sucralose, talc, titanium dioxide, triacetin and water.

FDA approved dissolution test and acceptance criterion differ from USP.

12 CLINICAL PHARMACOLOGY

12.1 Mechanism of Action

Malaria

Hydroxychloroquine is a 4-aminoquinoline antimalarial [see Microbiology (12.4)] and antirheumatic agent.

Rheumatoid Arthritis, Systemic Lupus Erythematosus and Chronic Discoid Lupus Erythematosus

The mechanisms underlying the anti-inflammatory and immunomodulatory effects of SOVUNA in the treatment of rheumatoid arthritis, chronic discoid lupus erythematosus and systemic lupus erythematosus are not fully known.

12.2 Pharmacodynamics

The exposure-response relationship and time course of pharmacodynamic response for the safety and effectiveness of hydroxychloroquine have not been fully characterized.

12.3 Pharmacokinetics

Following oral administration, the whole blood concentration of hydroxychloroquine at steady state is dose proportional over a dose range from 200 mg daily to 400 mg daily of hydroxychloroquine in rheumatoid arthritis and lupus patients.

Absorption

Following a single 200 mg oral dose of hydroxychloroquine to healthy male volunteers, whole blood hydroxychloroquine Cmax was 129.6 ng/mL (plasma Cmax was 50.3 ng/mL) with Tmax of 3.3 hours (plasma Tmax 3.7 hours). Peak blood concentrations of metabolites were observed at the same time as peak levels of hydroxychloroquine. Mean absolute oral bioavailability is 79% (SD: 12%) in fasting conditions.

Peak blood concentrations ranged from 1161 ng/mL to 2436 ng/mL (mean 1918 ng/mL) following a single dose of 155 mg intravenous infusion and from 2290 ng/mL to 4211 ng/mL (mean 3312 ng/mL) following a single dose of 310 mg intravenous infusion in healthy subjects. Pharmacokinetic parameters were not significantly different over the therapeutic dose range of 155 mg and 310 mg indicating linear kinetics.

In patients with rheumatoid arthritis, there was large variability as to the fraction of the dose absorbed (i.e., 30 to 100%), and mean hydroxychloroquine levels were significantly higher in patients with less disease activity.

Distribution

Hydroxychloroquine is extensively distributed to tissues and has a large volume of distribution. Approximately 50% of hydroxychloroquine is bound to plasma proteins.

Metabolism

Significant levels of three metabolites, desethylhydroxychloroquine (DHCQ), desethylchloroquine (DCQ), and bidesethylhydroxychloroquine (BDCQ) were found in plasma and blood, with DHCQ being the major metabolite. In vitro, hydroxychloroquine is metabolized mainly by CYP2C8, CYP3A4 and CYP2D6 as well as by FMO-1 and MAO-A.

Elimination / Excretion

Renal clearance in patients with rheumatoid arthritis treated with hydroxychloroquine for at least 6 months was similar to that in single dose studies in healthy volunteers, suggesting that no change in clearance occurred with chronic dosing. Renal clearance of unchanged hydroxychloroquine was approximately 16% to 30% of the dose after oral and IV administration. Results following a single oral dose of a 200 mg tablet demonstrated a half-life of hydroxychloroquine about 40 days in whole blood. Following chronic oral administration of hydroxychloroquine, the absorption half-life of hydroxychloroquine was approximately 3 to 4 hours and the terminal half-life ranged from 40 to 50 days in whole blood. The effective half-life of hydroxychloroquine is likely to be shorter and steady state is achieved by 6 weeks following 400 mg daily oral administration in rheumatoid arthritis patients.

Drug Interaction Studies

In vitro study suggested that hydroxychloroquine has a potential to inhibit CYP2D6, CYP3A4, P-glycoproteins (P-gp), MATE1 and MATE2-K.

In vitro study suggested that hydroxychloroquine has no significant potential to inhibit CYP1A2, CYP2B6, CYP2C8, CYP2C9, CYP2C19, and the main transporters OATP1B1, OATP1B3, OAT1, OAT3, OCT1, and OCT2. In vitro, hydroxychloroquine has no significant potential to induce CYP1A2, CYP2B6 and CYP3A4.

12.4 Microbiology

Mechanism of Action in Malaria

The precise mechanism by which hydroxychloroquine exhibits activity against Plasmodium is not known. Hydroxychloroquine is a weak base and may exert its effect by concentrating in the acid vesicles of the parasite and inhibiting polymerization of heme. It can also inhibit certain enzymes by its interaction with DNA.

Antimicrobial Activity

Hydroxychloroquine is active against the erythrocytic forms of chloroquine sensitive strains of P. falciparum, P. malariae, P. vivax, and P. ovale. Hydroxychloroquine is not active against the gametocytes and exoerythrocytic forms including the hypnozoite liver stage forms of P. vivax and P. ovale.

Drug Resistance

P. falciparum strains exhibiting reduced susceptibility to chloroquine also show reduced susceptibility to hydroxychloroquine. Resistance of Plasmodium parasites to chloroquine is widespread [see Indications and Usage (1.1)].

13 NONCLINICAL TOXICOLOGY

13.1 Carcinogenesis & Mutagenesis & Impairment Of Fertility

No carcinogenicity or genotoxicity studies have been conducted with hydroxychloroquine. No animal studies have been performed to evaluate the potential effects of hydroxychloroquine on reproduction or development, or to determine potential effects on fertility in males or females.

15 REFERENCES

^1Center for Disease Control and Prevention. Malaria.

https://www.cdc.gov/parasites/malaria/index.html

16 HOW SUPPLIED/STORAGE AND HANDLING

16.1 How Supplied

SOVUNA (hydroxychloroquine sulfate) Tablets are available in the following strengths and packing configurations:

- 200 mg of hydroxychloroquine sulfate: white to off-white, capsule-shaped, film-coated tablets, debossed with "172" on one side and plain on the other side.

Bottles of 30 tablets with child resistant closure (NDC 70954-804-10)

Bottles of 100 tablets with child resistant closure (NDC 70954-804-20)

- 300 mg of hydroxychloroquine sulfate: white to off-white, functionally scored, capsule-shaped, film-coated tablets, debossed with "1" on left side of the score and "71" on right side of the score and plain on the other side.

Bottles of 100 tablets with child resistant closure (NDC 70954-805-10)

16.2 Storage

Dispense in a tight, light-resistant container as defined in the USP/NF. Keep out of the reach of children.

Store at room temperature between 20°C and 25°C (68°F and 77°F), allow excursions between 15°C and 30°C (59°F and 86°F).

17 PATIENT COUNSELING INFORMATION

Important Administration Instructions

Advise the patient to take SOVUNA with food or milk and not to crush the tablet.

Cardiomyopathy and Ventricular Arrhythmias

Inform the patient that serious cardiac effects, life-threatening and fatal cases have been reported with use of SOVUNA. Advise patients to seek medical attention immediately if they experience any symptoms of heart rhythm changes including fast or irregular heartbeat, lightheadedness, dizziness, or syncope [see Warnings and Precautions (5.1)].

Retinal Toxicity

Inform the patient that irreversible retinal damage has been observed in some patients with the use of SOVUNA. Advise patients of the importance of the ophthalmology visits for monitoring their eyes. Instruct patients to seek medical attention promptly if they experience decreased vision or decreased dark adaptation [see Warnings and Precautions (5.2)].

Serious Skin Reactions

Inform the patient that severe, life-threatening skin reactions have been reported with the use of SOVUNA. Advise the patient to seek medical attention immediately if experiencing any of the following signs and symptoms: blisters on the skin, eyes, lips or in the mouth, itching or burning, with or without fever [see Warnings and Precautions (5.3)].

Hepatotoxicity Associated with Porphyria Cutanea Tarda

Inform the patient that liver toxicity has been reported when SOVUNA was used in patients with porphyria cutanea tarda. In some cases, PCT was diagnosed only after the occurrence of liver injury, when SOVUNA was prescribed for an approved indication. Advise the patient to seek medical attention if experiencing fatigue, rash, nausea, dark urine, or jaundice [see Warnings and Precautions (5.5)].

Skeletal Muscle Myopathy or Neuropathy

Inform the patient that muscle weakness and atrophy has been reported with SOVUNA use. Advise patients to report to the physician symptoms of muscle weakness [see Warnings and Precautions (5.8)].

Neuropsychiatric Reactions Including Suicidality

Alert patients to seek medical attention immediately if they experience new or worsening depression, suicidal thoughts, or other mood changes [see Warnings and Precautions (5.9)].

Hypoglycemia

Inform the patient that SOVUNA has been associated with severe hypoglycemia. Advise the patient to monitor blood sugar levels if possible and to seek medical attention if experiencing any of the signs and symptoms of hypoglycemia such as sweating, shakiness, weakness, dizziness, tachycardia, nausea, blurred vision, confusion, fainting, or loss of consciousness [see Warnings and Precautions (5.10)].

Pregnancy

Inform the patient that there is a pregnancy registry that monitors pregnancy outcomes in women exposed to SOVUNA during pregnancy. Encourage patients to register by contacting 1-877311-8972 [see Use in Specific Populations (8.1)].

SOVUNA® is a registered trademark of ANI Pharmaceuticals, Inc.

Distributed by:

ANI Pharmaceuticals, Inc.

Baudette, MN 56623

LB4637-03

PACKAGE LABEL.PRINCIPAL DISPLAY PANEL

SOVUNA (hydroxychloroquine sulfate) Tablets, 200 mg

NDC 70954-804-10 - Bottles of 30 tablets

SOVUNA (hydroxychloroquine sulfate) Tablets, 200 mg

NDC 70954-804-20 - Bottles of 100 tablets

SOVUNA (hydroxychloroquine sulfate) Tablets, 300 mg

NDC 70954-805-10 - Bottles of 100 tablets